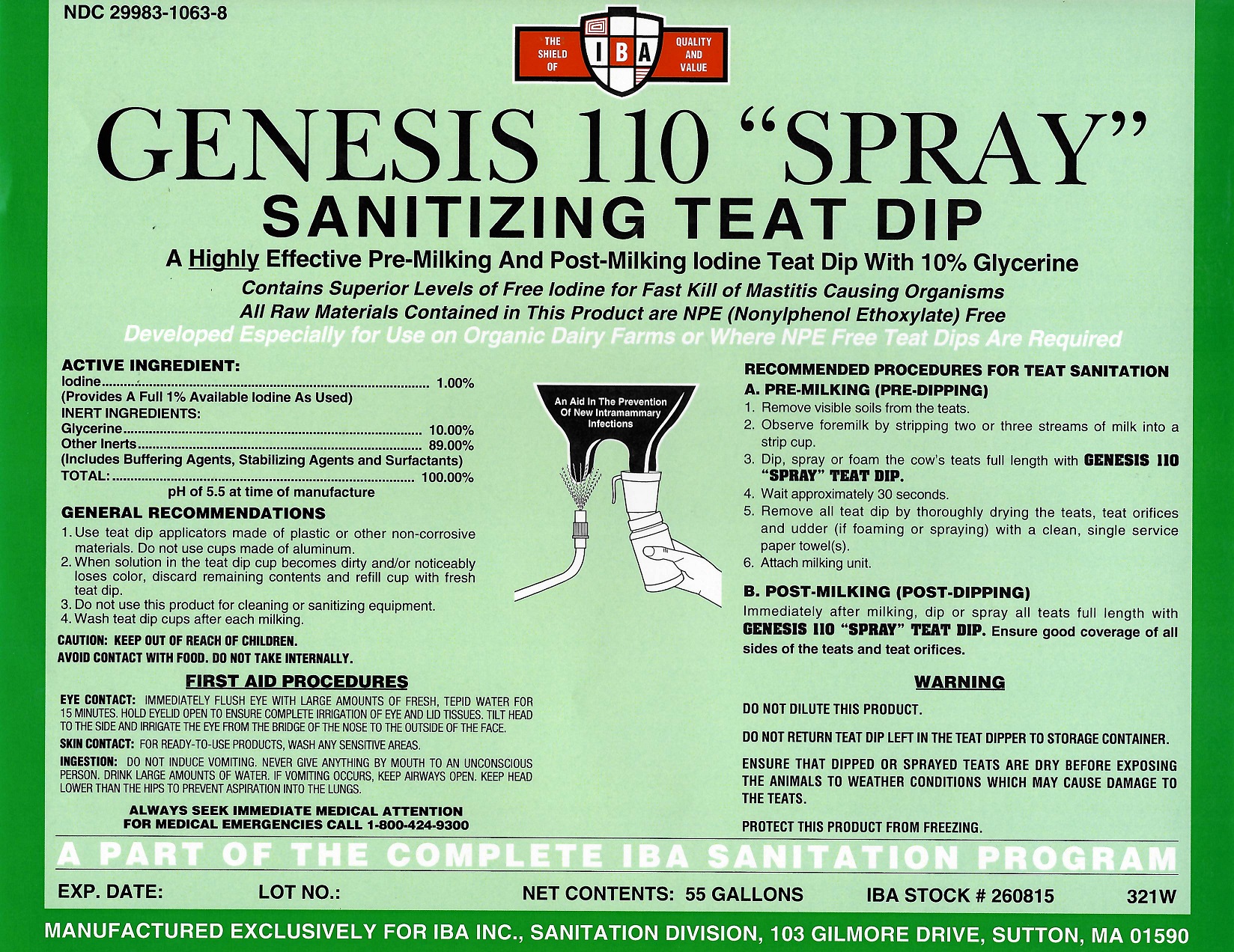 DRUG LABEL: Genesis 110 SPRA
NDC: 29983-1063 | Form: LIQUID
Manufacturer: IBA
Category: animal | Type: OTC ANIMAL DRUG LABEL
Date: 20251126

ACTIVE INGREDIENTS: iodine 1.0 kg/100 kg

Genesis 110 SPRAY

ACTIVE INGREDIENTS:

Iodine............................................................... 1.00%

(Provides A Full 1% Available Iodine As Used)

INERT INGREDIENTS:

Glycerine .......................................................... 10.00%
Other Inerts........... ......................................... 89.00%

(Includes Buffering Agents, Stabilizing Agents and Surfactants)
TOTAL: ............................................................. 100.00%

pH of 5.5 at the time of manufacture

GENERAL RECOMMENDATIONS

1. Use teat dip applicators made of plastic or other non-corrosive materials. Do not use cups made of aluminum.
2. When solution in the teat dip cup becomes dirty and/or noticeably loses color, discard remaining contents and refill cup with fresh teat dip.
3. Do not use this product for cleaning or sanitizing equipment.
4. Wash teat dip cups after each milking.

CAUTION

KEEP OUT OF REACH OF CHILDREN

CAUTION

AVOID CONTACT WITH FOOD. DO NOT TAKE INTERNALLY

INDICATIONS AND USAGE

RECOMMENDED PROCEDURES FOR TEAT SANITATION:
A. PRE-MILKING (PRE-DIPPING)
1. Remove visible soils from the teats.
2. Observe formilk by stripping two or three streams of milk into a strip cup.
3. Dip or spray the cow's teats full length with Genesis 110 “SPRAY” Teat Dip.
4. Wait approximately 30 seconds.
5. Remove all teat dip by thoroughly drying the teats and teat orifices and udder (if foaming or spraying) with a clean, single service paper towels(s).
6. Attach milking unit.
B. POST-MILKING (POST-DIPPING)
1. Immediately after milking, dip or spray all teats full length with Genesis 110 “SPRAY” Teat Dip. Ensure good coverage of all sides of the teats and teat orifices.

WARNING

DO NOT DILUTE THIS PRODUCT.

DO NOT RETURN TEAT DIP LEFT IN THE TEAT DIPPER TO STORAGE CONTAINER.

ENSURE THAT DIPPED OR SPRAYED TEATS ARE DRY BEFORE EXPOSING THE ANIMALS TO WEATHER CONDITIONS WHICH MAY CAUSE DAMAGE TO THE TEATS.

PROTECT THIS PRODUCT FROM FREEZING.